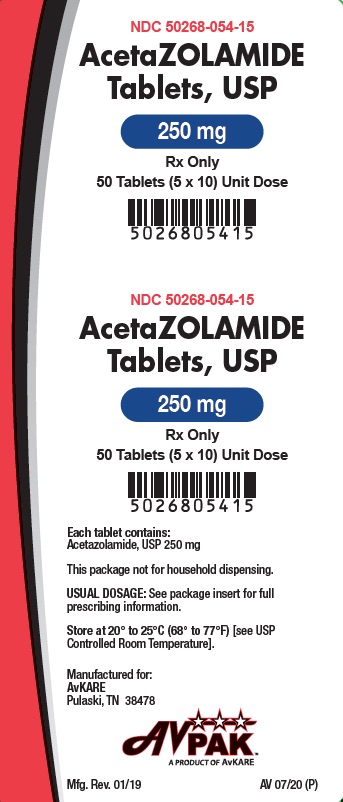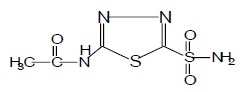 DRUG LABEL: Acetazolamide
NDC: 50268-054 | Form: TABLET
Manufacturer: AvPAK
Category: prescription | Type: HUMAN PRESCRIPTION DRUG LABEL
Date: 20260108

ACTIVE INGREDIENTS: ACETAZOLAMIDE 250 mg/1 1
INACTIVE INGREDIENTS: LACTOSE MONOHYDRATE; STARCH, CORN; GELATIN; GLYCERIN; WATER; SODIUM STARCH GLYCOLATE TYPE A POTATO; MAGNESIUM STEARATE; TALC

AcetaZOLAMIDE Tablets, USP
Rx only

DESCRIPTION

Acetazolamide an inhibitor of the enzyme carbonic anhydrase, is a white to faintly yellowish white crystalline, odorless powder, very slightly soluble in water, sparingly soluble in practically boiling water and slightly soluble in alcohol. The chemical name for acetazolamide is N-(5Sulfamoyl-1,3,4-thiadiazol-2-yl)-acetamide and has the following chemical structure:

Molecular Weight: 222.25

Molecular Formula: C4H6N4O3S2

Acetazolamide is available as oral tablets containing 125 mg and 250 mg of acetazolamide, respectively, and the following inactive ingredients: corn starch, gelatin, glycerin, lactose monohydrate, magnesium stearate, purified water, sodium starch glycolate (Potato) and talc.

CLINICAL PHARMACOLOGY

Acetazolamide is a potent carbonic anhydrase inhibitor, effective in the control of fluid secretion (e.g., some types ofglaucoma), in the treatment of certain convulsive disorders (e.g., epilepsy), and in the promotion of diuresis in instances of abnormal fluid retention (e.g., cardiac edema)

Acetazolamide is not a mercurial diuretic. Rather, it is a nonbacteriostatic sulfonamide possessing a chemical structure and pharmacological activity distinctly different from the bacteriostatic sulfonamides

Acetazolamide is an enzyme inhibitor that acts specifically on carbonic anhydrase, the enzyme that catalyzes the reversible reaction involving the hydration of carbon dioxide and the dehydration of carbonic acid. In the eye, this inhibitory action of acetazolamide decreases the secretion of aqueous humor and results in a drop in intraocular pressure, a reaction considered desirable in cases of glaucoma and even in certain nonglaucomatous conditions. Evidence seems to indicate that acetazolamide has utility as an adjuvant in the treatment of certain dysfunctions of the central nervous system (e.g., epilepsy). Inhibition of carbonic anhydrase in this area appears to retard abnormal, paroxysmal, excessive discharge from central nervous system neurons. The diuretic effect of acetazolamide is due to its action in the kidney on the reversible reaction involving hydration of carbon dioxide and dehydration of carbonic acid. The result is renal loss of HCO3 ion, which carries out sodium, water, and potassium. Alkalinization of the urine and promotion of diuresis are thus affected. Alteration in ammonia metabolism occurs due to increased reabsorption of ammonia by the renal tubules as a result of urinary alkalinization

Placebo-controlled clinical trials have shown that prophylactic administration of acetazolamide at a dose of 250 mg every eight to 12 hours (or a 500 mg controlled-release capsule once daily) before and during rapid ascentto altitude results in fewer and/or less severe symptoms (such as headache, nausea, shortness of breath, dizziness, drowsiness, and fatigue) of acute mountain sickness (AMS). Pulmonary function (e.g., minute ventilation, expired vital capacity and peak flow) is greater in the acetazolamide treated group, both in subjects with AMS and asymptomatic subjects. The acetazolamide treated climbers also had less difficulty in sleeping.

INDICATIONS AND USAGE

For adjunctive treatment of: edema due to congestive heart failure; drug-induced edema; centrencephalic epilepsies (petit mal, unlocalized seizures); chronic simple (open-angle) glaucoma, secondary glaucoma, and preoperatively in acute angle-closure glaucoma where delay of surgery is desired in order to lower intraocular pressure. Acetazolamide Tablets are also indicated for the prevention or amelioration of symptoms associated with acute mountain sickness in climbers attempting rapid ascent and in those who are very susceptible to acute mountain sickness despite gradual ascent.

CONTRAINDICATIONS

Acetazolamide therapy is contraindicated in situations in which sodium and/or potassium blood serum levels are depressed, in cases of marked kidney and liver disease or dysfunction, in suprarenal gland failure, and in hyperchloremic acidosis. It is contraindicated in patients with cirrhosis because of the risk of development of hepatic encephalopathy

Long-term administration of acetazolamide is contraindicated in patients with chronic non-congestive angle-closure glaucoma since it may permit organic closure of the angle to occur while the worsening glaucoma is masked by lowered intraocular pressure.

WARNINGS

Fatalities have occurred, although rarely, due to severe reactions to sulfonamides including Stevens-Johnson syndrome, toxic epidermal necrolysis, fulminant hepatic necrosis, agranulocytosis, aplastic anemia, and other blood dyscrasias. Sensitizations may recur when a sulfonamide is readministered irrespective of the route of administration. If signs of hypersensitivity or other serious reactions occur, discontinue use of this drug

Caution is advised for patients receiving concomitant high-dose aspirin and acetazolamide, as anorexia, tachypnea, lethargy, coma and death have been reported.

PRECAUTIONS

General

Increasing the dose does not increase the diuresis and may increase the incidence of drowsiness and/or paresthesia. Increasing the dose often results in a decrease in diuresis. Under certain circumstances, however, very large doses have been given in conjunction with other diuretics in order to secure diuresisin complete refractory failure.

Information for Patients

Adverse reactions common to all sulfonamide derivatives may occur: anaphylaxis, fever, rash (including erythema multiforme, Stevens-Johnson syndrome, toxic epidermal necrolysis), crystalluria, renal calculus, bone marrow depression, thrombocytopenic purpura, hemolytic anemia, leukopenia, pancytopenia and agranulocytosis. Precaution is advised for early detection of such reactions and the drug should be discontinued and appropriate therapy instituted

In patients with pulmonary obstruction or emphysema where alveolar ventilation may be impaired, acetazolamide, which may precipitate or aggravate acidosis, should be used with caution

Gradual ascent is desirable to try to avoid acute mountain sickness. If rapid ascent is undertaken and acetazolamide tablets are used, it should be noted that such use does not obviate the need for prompt descent if severe forms of high altitude sickness occur, i.e., high altitude pulmonary edema(HAPE) or high altitude cerebral edema

Caution is advised for patients receiving concomitant high-dose aspirin and acetazolamide, as anorexia, tachypnea, lethargy, coma and death have been reported (see WARNINGS).

Laboratory Tests

To monitor for hematologic reactions common to all sulfonamides, it isrecommended that a baseline CBC and platelet count be obtained on patients prior to initiating acetazolamide tablet therapy and at regular intervals during therapy. If significant changes occur, early discontinuance and institution of appropriate therapy are important. Periodic monitoring of serum electrolytes is recommended.

Carcinogenesis , Mutagenesis , Impairment of Fertility

Long-term studies in animals to evaluate the carcinogenic potential of acetazolamide have not been conducted. In a bacterial mutagenicity assay, acetazolamide was not mutagenic when evaluated with and without metabolic activation

The drug had no effect on fertility when administered in the diet to male and female rats at a daily intake of up to 4 times the recommended human dose of 1000 mg in a 50 kg individual.

Pregnancy

Teratogenic Effects

Pregnancy Category C

Acetazolamide, administered orally or parenterally, has been shown to be teratogenic (defects of the limbs) in mice, rats, hamsters and rabbits. There are no adequate and well-controlled studies in pregnant women. Acetazolamide should be used in pregnancy only if the potential benefit justifies the potential risk to the fetus.

Nursing Mothers

Because of the potential for serious adverse reaction in nursing infants from acetazolamide, a decision should be made whether to discontinue nursing or to discontinue the drug taking into account the importance of the drug to the mother.

Pediatric Use

The safety and effectiveness of acetazolamide in pediatric patients has not been established.

ADVERSE REACTIONS

Adverse reactions, occurring most often early in therapy, include paresthesias, particularly a "tingling" feeling in the extremities, hearing dysfunction or tinnitus, loss of appetite, taste alteration and gastrointestinal disturbances such as nausea, vomiting and diarrhea, polyuria, and occasional instances of drowsiness and confusion

Metabolic acidosis and electrolyte imbalance may occur

Transient myopia has been reported. This condition invariably subsides upon diminution or discontinuance of the medication

Other occasional adverse reactions include urticaria, melena, hematuria, glycosuria, hepatic insufficiency, flaccid paralysis, photosensitivity and convulsions. Also see PRECAUTIONS: Information for Patients for possible reactions common to sulfonamide derivatives. Fatalities have occurred although rarely, due to severe reactions to sulfonamides including Stevens-Johnson syndrome, toxic epidermal necrolysis, fulminant hepatic necrosis, agranulocytosis, aplastic anemia and other blood dyscrasias (see WARNINGS).

To report SUSPECTED ADVERSE REACTIONS contact AvKARE at 1-855-361-3993; email drugsafety@avkare.com; or FDA at 1-800-FDA-1088 or www.fda.gov/medwatch.

OVERDOSAGE

No data are available regarding acetazolamide overdosage in humans as no cases of acute poisoning with this drug have been reported. Animal data suggest that acetazolamide is remarkably nontoxic. No specific antidote is known. Treatment should be symptomatic and supportive

Electrolyte imbalance, development of an acidotic state, and central nervous effects might be expected to occur. Serum electrolyte levels (particularly potassium) and blood pH levels should be monitored

Supportive measures are required to restore electrolyte and pH balance. The acidotic state can usually be corrected by the administration of bicarbonate

Despite its high intraerythrocytic distribution and plasma protein binding properties, acetazolamide may be dialyzable. This may be particularly important in the management of acetazolamide overdosage when complicated by the presence of renal failure.

DOSAGE AND ADMINISTRATION

Glaucoma

Acetazolamide should be used as an adjunct to theusual therapy. The dosage employed in the treatment of chronic simple(open-angle) glaucoma ranges from 250 mg to 1 g of acetazolamide per 24hours, usually in divided doses for amounts over 250 mg. It has usually beenfound that a dosage in excess of 1 g per 24 hours does not produce an increased effect. In all cases, the dosage should be adjusted with careful individual attention both to symptomatology and ocular tension. Continuous supervision by a physician is advisable.

In treatment of secondary glaucoma and in the preoperative treatment of some cases of acute congestive (closed-angle) glaucoma, the preferred dosage is 250 mg every four hours, although some cases have responded to 250 mg twice daily on short-term therapy. In some acute cases, it may be more satisfactory to administer an intial dose of 500 mg followed by 125 mg or 250 mg every four hours depending on the individual case. A complementary effect has been noted when acetazolamide has been used in conjuction with miotics or mydriatics as the case demanded

Epilepsy

It is not clearly known whether the beneficial effects observed in epilepsy are due to direct inhibition of carbonic anhydrase in the central nervous system or whether they are due to the slight degree of acidosis produced by the divided dosage. The best results to date have been seen in petit mal in children.Good results, however, have been seen in patients, both children and adult, in other types of seizures such as grand mal, mixed seizure patterns, myoclonic jerk patterns, etc. The suggested total daily dose is 8 to 30 mg per kg in divided doses. Although some patients respond to a low dose, the optimum range appears to be from 375 to 1000 mg daily. However, some investigators feel that daily doses in excess of 1 g do not produce any better results than a 1 g dose.When acetazolamide tablets are given in combination with other anticonvulsants, it is suggested that the starting dose should be 250 mg once daily in addition to the existing medications. This can be increased to levels as indicated above

The change from other medications to acetazolamide should be gradual and in accordance with usual practice in epilepsy therapy

Congestive Heart Failure

For diuresis in congestive heart failure, the starting dose is usually 250 to 375 mg once daily in the morning (5 mg/kg). If, after an initial response, the patient fails to continue to lose edema fluid, do not increase the dose but allow for kidney recovery by skipping medication for a day

Acetazolamide tablets yield best diuretic results when given on alternate days, or for two days alternating with a day of rest

Failures in therapy may be due to overdosage or too frequent dosage. The use of acetazolamide does not eliminate the need for other therapy such as digitalis, bed rest, and salt restriction

Drug-Induced Edema

Recommended dosage is 250 to 375 mg of acetazolamide once a day for one or two days, alternating with a day of rest

Acute Mountain Sickness

Dosage is 500 mg to 1000 mg daily, in divided doses. In circumstances of rapid ascent, such as in rescue or military operations, the higher dose level of 1000 mg is recommended. It is preferable to initiate dosing 24 to 48 hours before ascent and to continue for 48 hours while at high altitude, or longer as necessary to control symptoms

Note: The dosage recommendations for glaucoma and epilepsy differ considerably from those for congestive heart failure, since the first two conditions are not dependent upon carbonic anhydrase inhibition in the kidney which requires intermittent dosage if it is to recover from the inhibitory effect of the therapeutic agent.

HOW SUPPLIED

Acetazolamide Tablets USP are supplied as follows:

125 mg – White to off white, round, flat, uncoated tablet, debossed as "S;571" on one side and scored in half on other side

250 mg – White to off white, round, biconvex, uncoated tablet, debossed as "S;572" on one side and scored in quarters on other side

NDC 50268-054-15 (10 tablets per card, 5 cards per carton).

Store at 20° to 25°C (68° to 77°F) [see USP Controlled Room Temperature]

For Institutional Use Only. Dispensed in Unit Dose Package.

Manufactured for:

AvKARE

Pulaski, TN 38478

Mfg. Rev. 01/19

AV 07/20 (P)

AvPAK